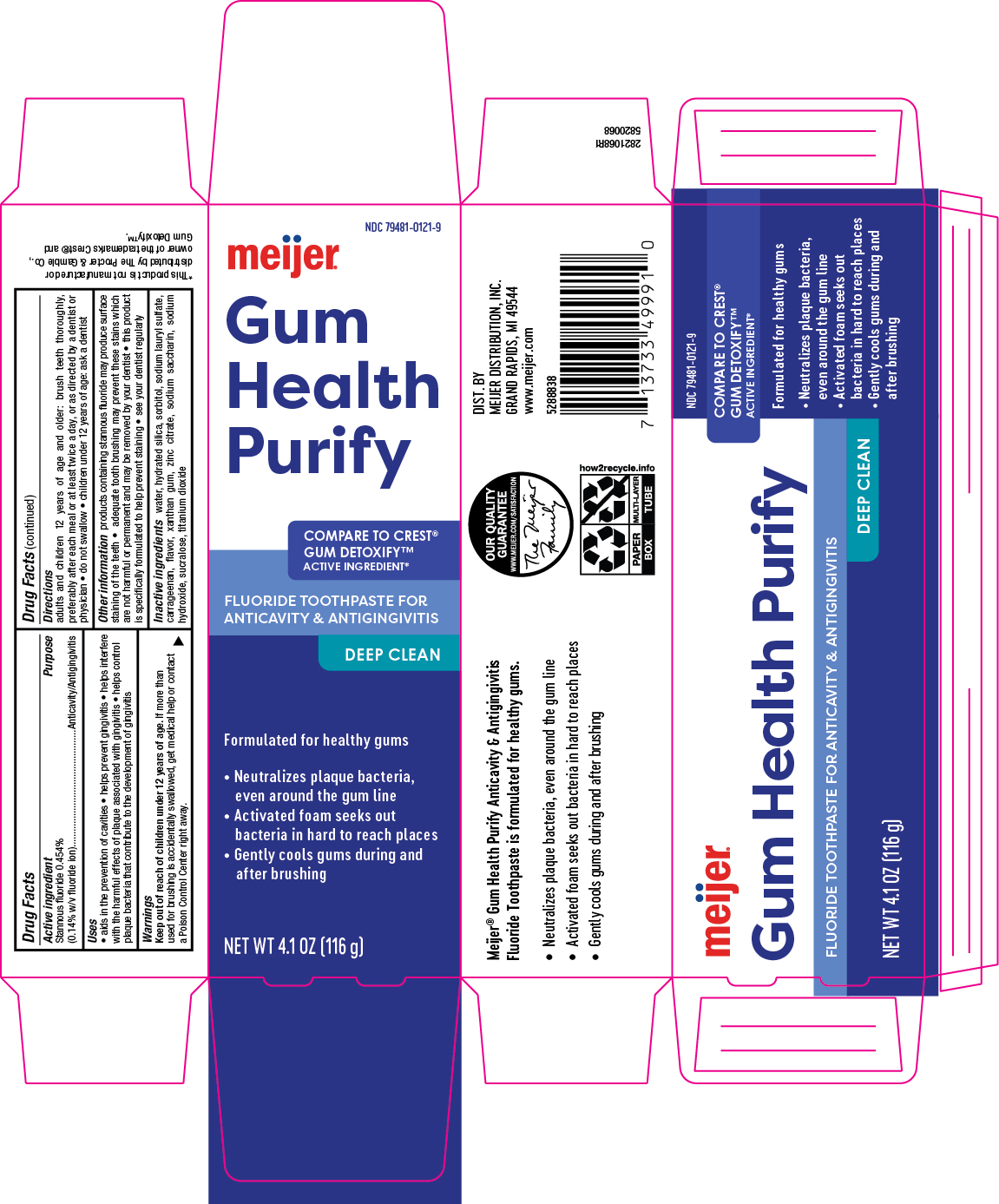 DRUG LABEL: Gum Detoxify
NDC: 79481-0121 | Form: GEL, DENTIFRICE
Manufacturer: Meijer, Inc.
Category: otc | Type: HUMAN OTC DRUG LABEL
Date: 20251113

ACTIVE INGREDIENTS: STANNOUS FLUORIDE 0.14 g/100 g
INACTIVE INGREDIENTS: SACCHARIN SODIUM; SODIUM HYDROXIDE; XANTHAN GUM; SORBITOL; SUCRALOSE; TITANIUM DIOXIDE; HYDRATED SILICA; ZINC CITRATE; SODIUM LAURYL SULFATE; WATER; CARRAGEENAN

5820068 Meijer Gum Detoxify

Active ingredient

Stannous fluoride 0.454% (0.14% w/v fluoride ion)

Purpose

Anticavity/Antigingivitis

Uses

aids in the prevention of cavities * helps prevent gingivitis * helps interfere with teh harmful effects of plaque associated with gingivitis * helps control plaque bacteria that contribute to teh development of gingivitis

Warnings

Keep out of reach of children under 12 years of age. If more than used for brushing is accidentally swallowed, get medical help or contact a Poison Control Center (1-800-222-1222) right away.

Keep out of reach of children under 12 years of age

If more than used for brushing is accidentally swallowed, get medical help or contact a Poison Control Center (1-800-222-1222) right away.

Directions

adults and children 12 years of age and older: brush teeth thoroughly, preferably after each meal or at least twice a day, or as directed by a dentist or physician * do not swallow * children under 12 years of age: ask a dentist

Other information

products containing stannous fluoride may produce surface staining of the teeth * adequate tooth brushing may prevent these stains which are not harmful or permanent and may be removed by your dentist * this product is specifically formulated to help prevent staining * see your dentist regularly

Inactive ingredients

water, hydrated silica, sorbitol, sodium lauryl sulfate, carrageenan, flavor, xanthan gum, zinc citrate, sodium saccharin, sodium hydroxide, sucralose, titanium dioxide